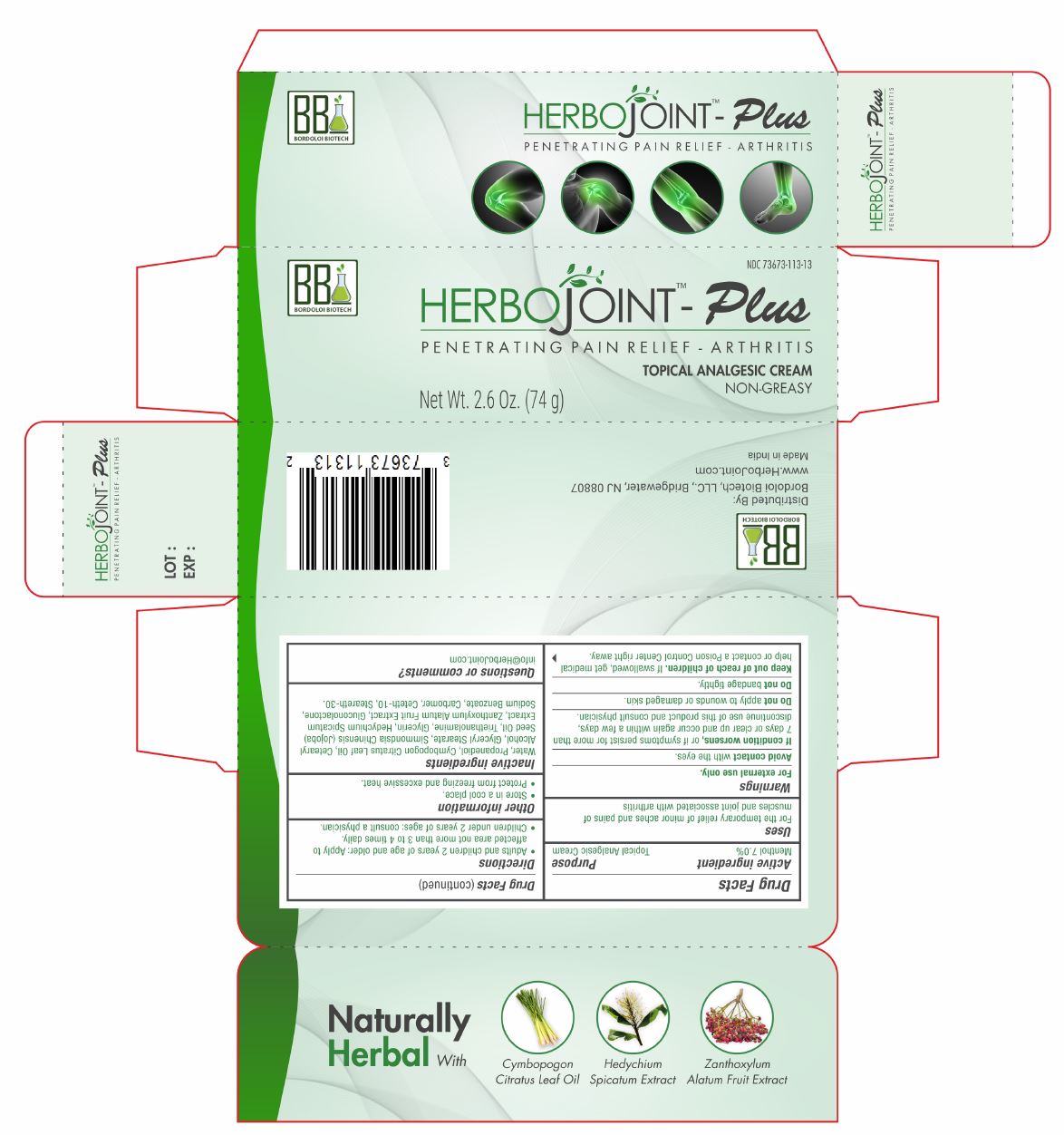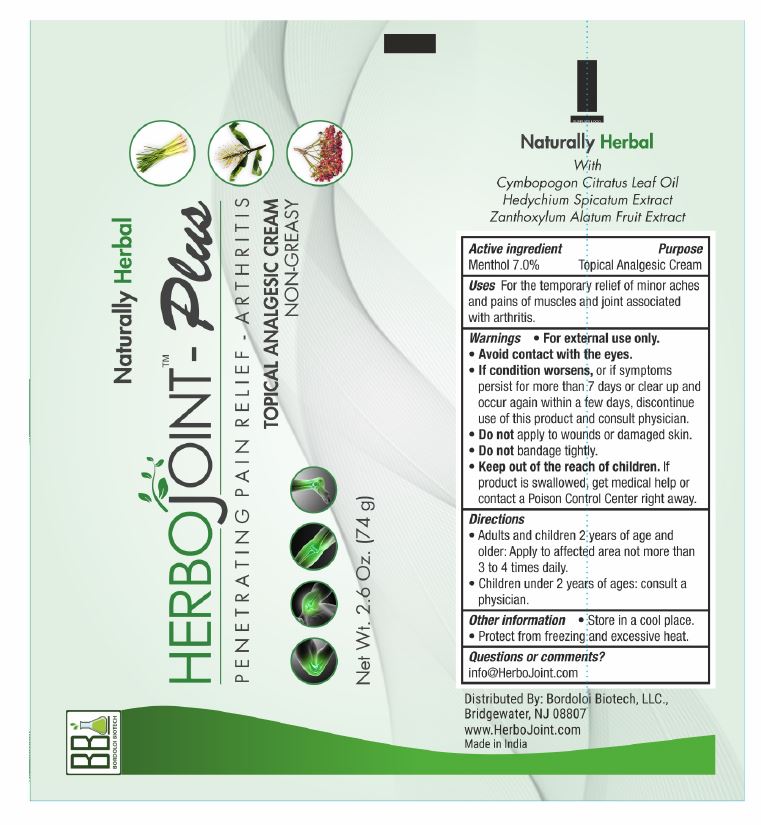 DRUG LABEL: HERBOJOINT-US
NDC: 73673-113 | Form: CREAM
Manufacturer: Bordoloi Biotech, LLC.
Category: otc | Type: HUMAN OTC DRUG LABEL
Date: 20210720

ACTIVE INGREDIENTS: MENTHOL 70 mg/1 g
INACTIVE INGREDIENTS: WATER; PROPANEDIOL; CYMBOPOGON CITRATUS LEAF; CETOSTEARYL ALCOHOL; GLYCERYL MONOSTEARATE; JOJOBA OIL; TROLAMINE; GLYCERIN; HEDYCHIUM SPICATUM ROOT; ZANTHOXYLUM ARMATUM FRUIT; GLUCONOLACTONE; SODIUM BENZOATE; CARBOMER HOMOPOLYMER, UNSPECIFIED TYPE; CETETH-10; STEARETH-30

HERBOJOINT-US

Active Ingredient Purpose
Menthol 7.0% Topical Analgesic Cream

Purpose:
Penetrating Pain Relief-Arthritis

Uses

For the temporary relief of minor aches and pains of muscles and joint associated with arthritis

Warnings

- For external use only.
- Avoid contact with the eyes.
- If condition worsens, or if symptoms persist for more than 7 days or clear up and occur again within a few days, discontinue use of this product and consult physician.
- Do not apply to wounds or damaged skin.
- Do not bandage tightly.

KEEP OUT OF REACH OF CHILDREN

Keep out of the reach of children. If swallowed, get medical help or contact a Poison Control Center right away.

Directions:

- Adults and children 2 years of age and older: Apply to affected area not more than 3 to 4 times daily.
- Children under 2 years of ages: consult a physician.

Other information

- Store in a cool place.
- Protect from freezing and excessive heat.

Inactive ingredients:

Water, Propanediol, Cymbopogon Citratus Leaf Oil, Cetearyl Alcohol, Glyceryl Stearate, Simmondsia Chinensis (Jojoba) Seed Oil, Triethanolamine, Glycerin, Hedychium Spicatum Extract, Zanthoxylum Alatum Fruit Extract, Gluconolactone, Sodium Benzoate, Carbomer, Ceteth-10, Steareth-30.

HOW SUPPLIED

Distributed By:
Bordoloi Biotech, LLC., Bridgewater, NJ 08807

www.HerboJoint.com
Made in India